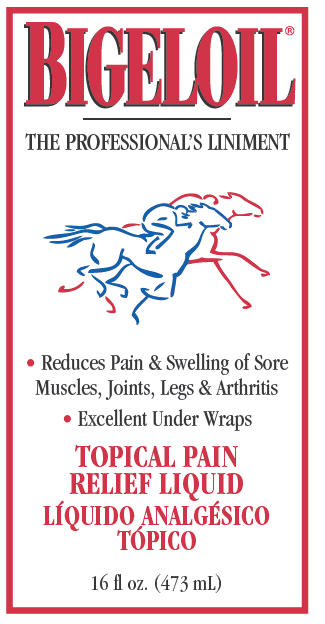 DRUG LABEL: Bigeloil
NDC: 11444-130 | Form: LIQUID
Manufacturer: W. F. Young, Inc.
Category: animal | Type: OTC ANIMAL DRUG LABEL
Date: 20241101

ACTIVE INGREDIENTS: MENTHOL, UNSPECIFIED FORM 1.25 g/115 mL

BIGELOIL®
The Professional Liniment

Can be used before, during and after competition

Can also be used on dogs

Indications

For temporary relief of minor pain and swelling from sprains, strains, bruises, arthritis, overworked muscles and minor wounds.

Directions for Use

Rub onto sore area 2 to 3 times a day. For faster relief, rub with hair and wrap or blanket, especially overnight. Body Wash: mix 2 to 4 oz. with 1 gal. water, apply with sponge, avoid eyes. Brace: mix 2 to 3 oz. with 1 quart water, apply with sponge to warm horse up before workout, avoid eyes and saddle area. Arthritis: rub onto knees, hocks and fetlocks before workout, apply again at night and lightly wrap. Antiseptic: for minor wounds and skin irritations, apply full strength without rubbing.

Caution: Avoid contact with eyes and mucous membranes. Stop using if skin irritation develops or symptoms persist for more than 10 days. For severe injuries consult a veterinarian. For external use only. Keep out of reach of children.

Warning

Flammable. Keep away from fire, sparks and heated surfaces. Store at room temperature. For animal use only.

Active Ingredients

Menthol 1.25% W/W.

Other Ingredients

Alcohol, D&C Green #5, FD&C Yellow #5, Fragrance, Juniperberry Oil, Methyl Salicylate, Salicylic Acid, Thymol and Purified Water.

Distributed by:
W. F. Young, Inc.
302 Benton Drive
E. Longmeadow, MA 01028 USA
© WFY
www.absorbine.com
RM 342328-3

PRINCIPAL DISPLAY PANEL - 473 mL Bottle Label

BIGELOIL®

THE PROFESSIONAL'S LINIMENT

• Reduces Pain & Swelling of Sore
Muscles, Joints, Legs & Arthritis

• Excellent Under Wraps

TOPICAL PAIN
RELIEF LIQUID

16 fl oz. (473 mL)